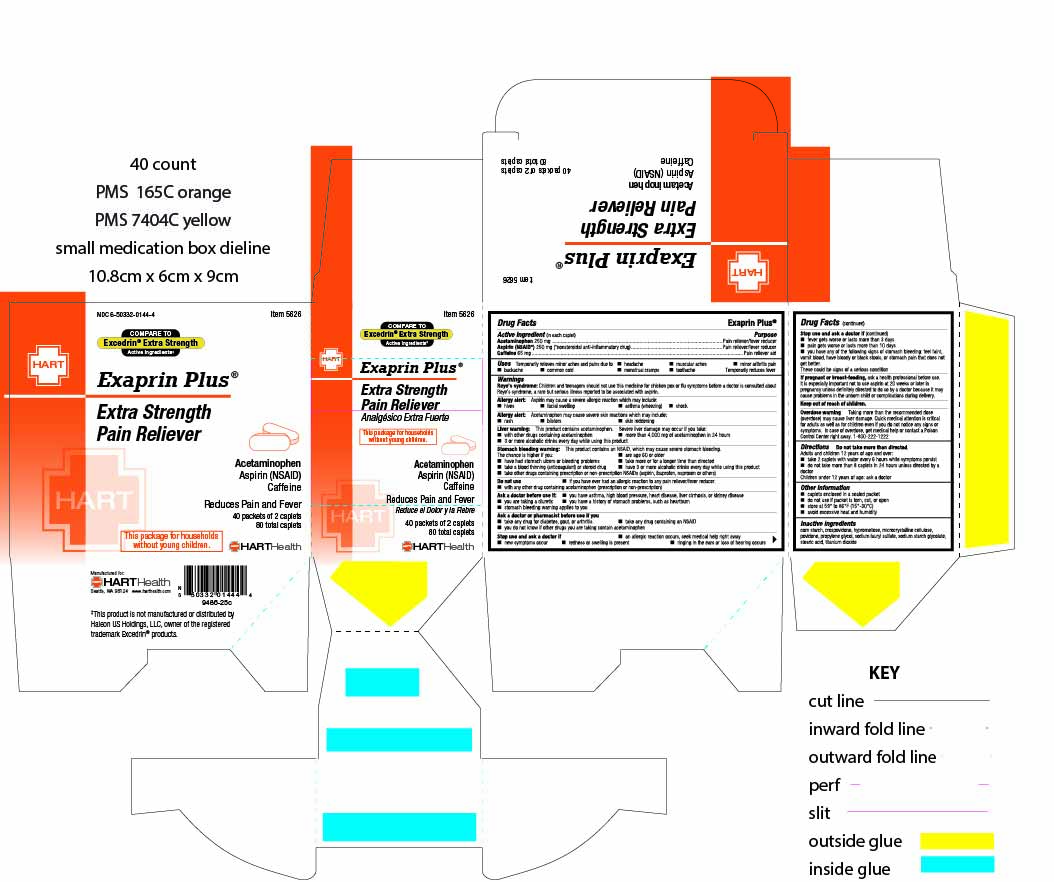 DRUG LABEL: Exaprin Plus
NDC: 50332-0144 | Form: TABLET, FILM COATED
Manufacturer: HART Health
Category: otc | Type: HUMAN OTC DRUG LABEL
Date: 20250804

ACTIVE INGREDIENTS: ACETAMINOPHEN 250 mg/1 1; ASPIRIN 250 mg/1 1; CAFFEINE 65 mg/1 1
INACTIVE INGREDIENTS: CROSPOVIDONE; HYPROMELLOSES; MICROCRYSTALLINE CELLULOSE; POVIDONE; PROPYLENE GLYCOL; SODIUM LAURYL SULFATE; STEARIC ACID; TITANIUM DIOXIDE

Exaprin Plus

Active ingredients (in each caplet)

Acetaminophen 250 mg
Aspirin 250 mg (*nonsteroidal anti-inflammatory drug)
Caffeine 65 mg

Purpose

Pain reliever
Pain reliever
Pain reliever aid

Uses

temporarily relieves minor aches and pains due to:

- headache
- muscular aches
- minor arthritis pain
- backache
- common cold
- menstrual cramps
- toothache
- temporarily reduces fever

Warning

Reye’s syndrome: Children and teenagers should not use this medicine for chicken pox or flu symptoms before a doctor is consulted about Reye's syndrome, a rare but serious illness reported to be associated with asprin.

Allergy alert: Aspirin may cause a severe allergic reaction which may include:

- hives
- facial swelling
- asthma (wheezing)
- shock

Allergy alert: Acetaminophen may cause severe skin reactions which may include:

- rash
- blisters
- skin reddening

Liver warning: This product contains acetaminophen. Severe liver damage may occur if you take:

- with other drugs containing acetaminophen
- more than 4,000 mg of acetaminophen in 24 hours
- 3 or more alcoholic drinks every day while using this product

Stomach bleeding warning: This product contains an NSAID, which may cause severe stomach bleeding.

The chance is higher if you:

- are age 60 or older
- have had stomach ulcers or bleeding problems
- take more or for a longer time than directed
- take a blood thinning (anticoagulant) or steroid drug
- have 3 or more alcoholic drinks every day while using this product
- take other drugs containing prescription or nonprescription NSAIDs (aspirin, ibuprofen, naproxen, or others)

Do not use

- if you have ever had an allergic reaction to any other pain reliever/fever reducer
- with any other drug containing acetaminophen (prescription or nonprescription).

Ask a doctor before use if

- you have asthma, high blood pressure, heart disease, liver cirrhosis, or kidney disease
- you are taking a diuretic
- you have a history of stomach problems, such as heartburn
- stomach bleeding warning applies you

Ask a doctor or pharmacist before use if you

- take any drug for diabetes, gout, or arthritis
- take any drug containing an NSAID
- you do not know if other drugs you are taking contain acetaminophen

Stop use and ask a doctor if

- an allergic reaction occurs, seek medical help right away
- new symptoms occur
- redness or swelling is present
- ringing in the ears or loss of hearing occurs
- fever gets worse or lasts more than 3 days
- pain gets worse or lasts more than 10 days
- you have any of the following signs of stomach bleeding: feel faint, vomit blood, have bloody or black stools, or stomach pain that does not get better.

These could be signs of a serious condition

If pregnant or breast-feeding,

ask a health professional before use. It is especially important not to use aspirin at 20 weeks or later in pregnancy unless definitely directed to do so by a doctor because it may cause problems in the unborn child or complications during delivery.

OVERDOSAGE

Overdose warning

taking more than the recommended dose (overdose) may cause liver damage. Quick medical attention is critical for adult as well as for children even if you do not notice any signs or symptoms. In case of overdose, get medical help or contact a Poison Control Center right away. 1-800-222-1222

Directions

do not take more than directed

Adults and children 12 years of age and over:

- take 2 caplets with water every 6 hours while symptoms persist
- do not take more than 8 caplets in 24 hours unless directed by a doctor.

Children under 12 years of age: ask a doctor

Other information

- caplets enclosed in a sealed packet
- do not use if packet is torn, cut, or open
- store at 59° to 86°F (15°-30°C)
- avoid excessive heat and humidity

Inactive ingredients

corn starch, crospovidone, hypromellose, microcrystalline cellulose, povidone, propylene glycol, sodium lauryl sulfate, sodium starch glycolate, stearic acid, titanium dioxide